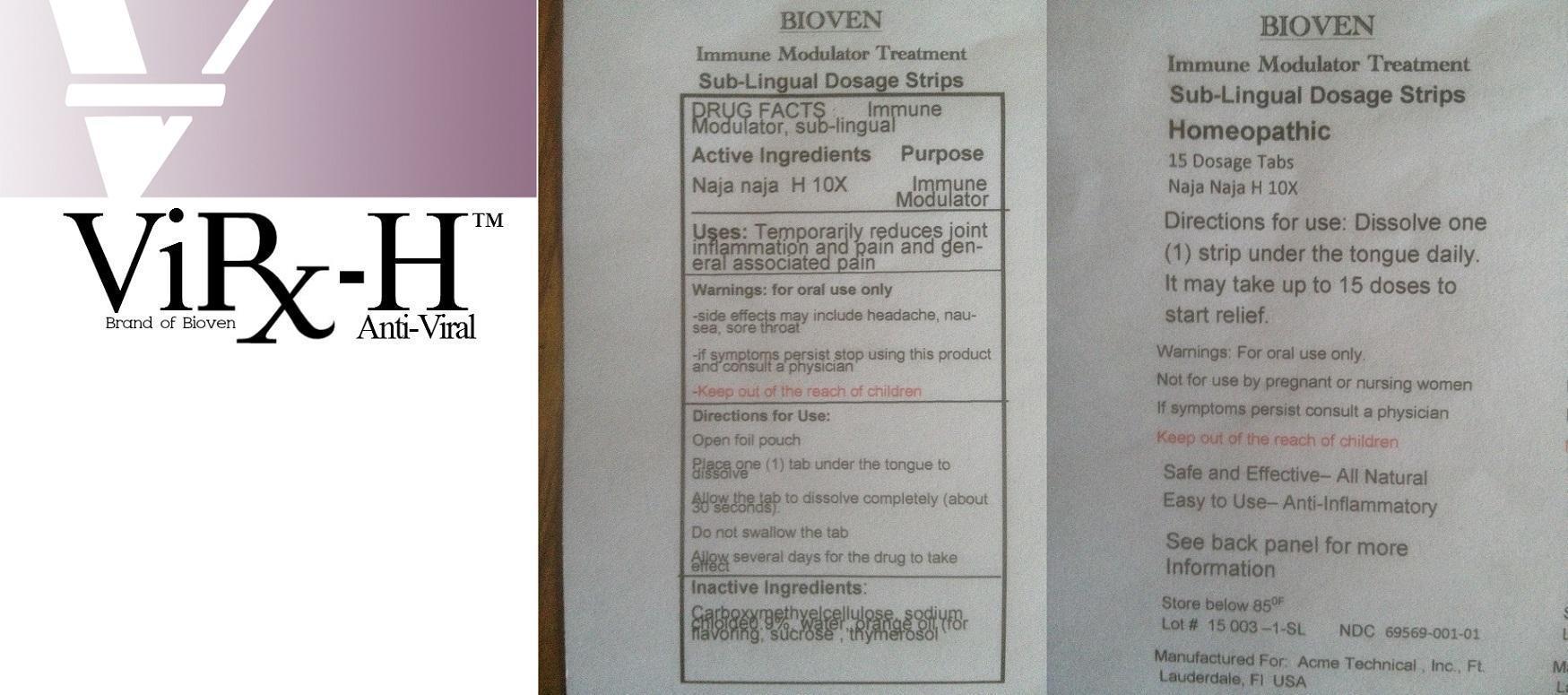 DRUG LABEL: VIRx-H
NDC: 69792-000 | Form: TABLET
Manufacturer: Medforce Solutions Inc.
Category: homeopathic | Type: HUMAN OTC DRUG LABEL
Date: 20150514

ACTIVE INGREDIENTS: NAJA NAJA VENOM 10 [hp_X]/1 1
INACTIVE INGREDIENTS: CARBOXYMETHYLCELLULOSE; SODIUM CHLORIDE; WATER; ORANGE OIL; SUCROSE; THIMEROSAL

Active Ingredients Purpose

Naja naja H 10X Immune Modulator

PURPOSE

Uses: Temporarily reduces joint inflammation and pain and general associated pain

-Keep out of the reach of children

INDICATIONS AND USAGE

ViRx-H

Anti-Viral

Brand of Bioven

DOSAGE AND ADMINISTRATION

Directions for Use:

Open foil pouch

Place one (1) tab under the tongue to dissolve

Allow the tab to dissolve completely (about 30 seconds).

Do not swallow the tab

Allow several days for the drug to take effect

Warnings: for oral use only

-side effects may include headache, nausea, sore throat

-if symptoms persist stop using this product and consult a physician

Inactive Ingredients:

carboxymethylcellulose, sodium chloride 0.9%, water, orange oil (for flavoring), sucrose, thymerosol